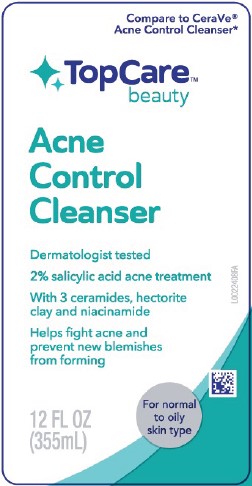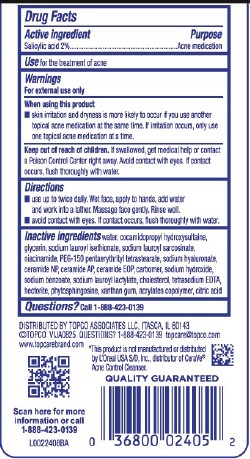 DRUG LABEL: Salicylic acid
NDC: 76162-414 | Form: LIQUID
Manufacturer: Topco Associates LLC
Category: otc | Type: HUMAN OTC DRUG LABEL
Date: 20260206

ACTIVE INGREDIENTS: SALICYLIC ACID 20 mg/1 mL
INACTIVE INGREDIENTS: CERAMIDE 1; HYALURONATE SODIUM; CERAMIDE NP; CERAMIDE AP; CARBOMER HOMOPOLYMER, UNSPECIFIED TYPE; GLYCERIN; SODIUM LAUROYL SARCOSINATE; PEG-150 PENTAERYTHRITYL TETRASTEARATE; HECTORITE; PHYTOSPHINGOSINE; EDETATE SODIUM; XANTHAN GUM; COCAMIDOPROPYL HYDROXYSULTAINE; SODIUM LAUROYL LACTYLATE; WATER; SODIUM LAUROYL ISETHIONATE; NIACINAMIDE; SODIUM HYDROXIDE; CITRIC ACID; BUTYL ACRYLATE/METHYL METHACRYLATE/METHACRYLIC ACID COPOLYMER (18000 MW); SODIUM BENZOATE; CHOLESTEROL

Top Care 414.000/414AA
Acne Control Cleanser

Active ingredient

Salicylic acid 2%

Purpose

Acne medication

Use

for the treatment of acne

Warnings

For external use only

When using this product

- skin irritation and dryness is more likely to occur if you use another topical acne medication at the same time. If irritation occurs, only use one topical acne medication at a time.

Keep out of reach of children.

If swallowed, get medical help or contact a Poison Control Center right away. Avoid contact with eyes. If contact occurs, flush thoroughly with water.

Directions

- use up to twice daily. Wet face, apply to hands, add water and work into a lather. Massage face gently. Rinse well.
- avoid contact with eyes. If contact occurs, flush thoroughly with water.

Inactive ingredients

water, cocamidopropyl hydroxysultaine, glycerin, sodium lauroyl isethionate, sodium lauroyl sarcosinate, niacinamide, PEG-150 pentaerythrityl tetrastearate, sodium hyaluronate, ceramide NP, ceramide AP, ceramide EOP, carbomer, sodium hydroxide, sodium benzoate, sodium lauroyl lactylate, cholesterol, tetrasodium EDTA, hectorite, phytosphingosine, xanthan gum, acrylates copolymer, citric acid

Questions?

Call 1-888-423-0139

Adverse Reaction

DISTRIBUTED BY TOPCO ASSOCIATES LLC, ITASCA, IL 60143

©TOPCO VIJA0825 QUESTIONS? 1-888-423-0139 topcare@topco.com

www.topcarebrand.com

Scan here for more information 1-888-423-0139

QUALITY GUARANTEED

Disclaimer

*This product is not manufactured or distributed by L'Oreal USA S/D, Inc., distributor of CeraVe® Acne Control Cleanser.

Principal Display Panel

Compare to CeraVe® Acne Control Cleanser*

Top Care™ beauty

Acne Control Cleanser

Dermatologist tested

2% salicylic acid acne treatment

With 3 ceramides, hectorite clay and niacinamide

Helps fight acne and prevent new blemishes from forming

For normal to oily skin type

12 FL OZ (355 mL)